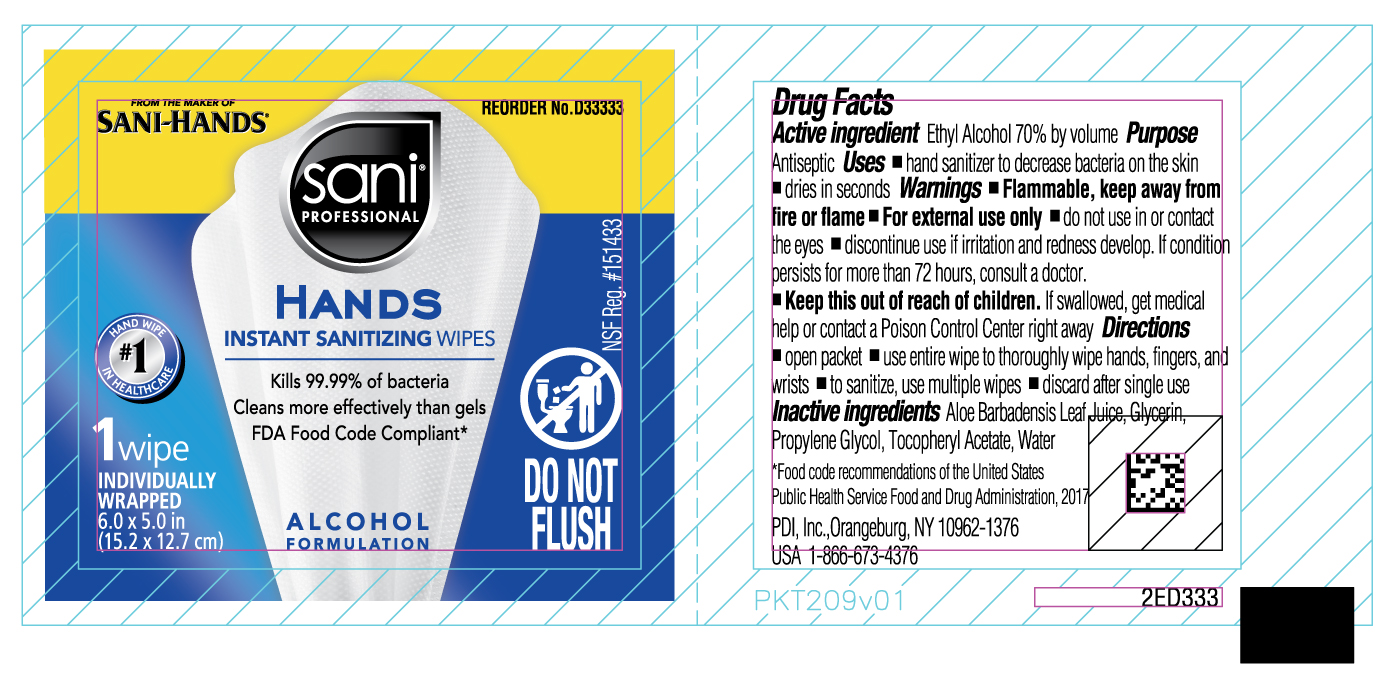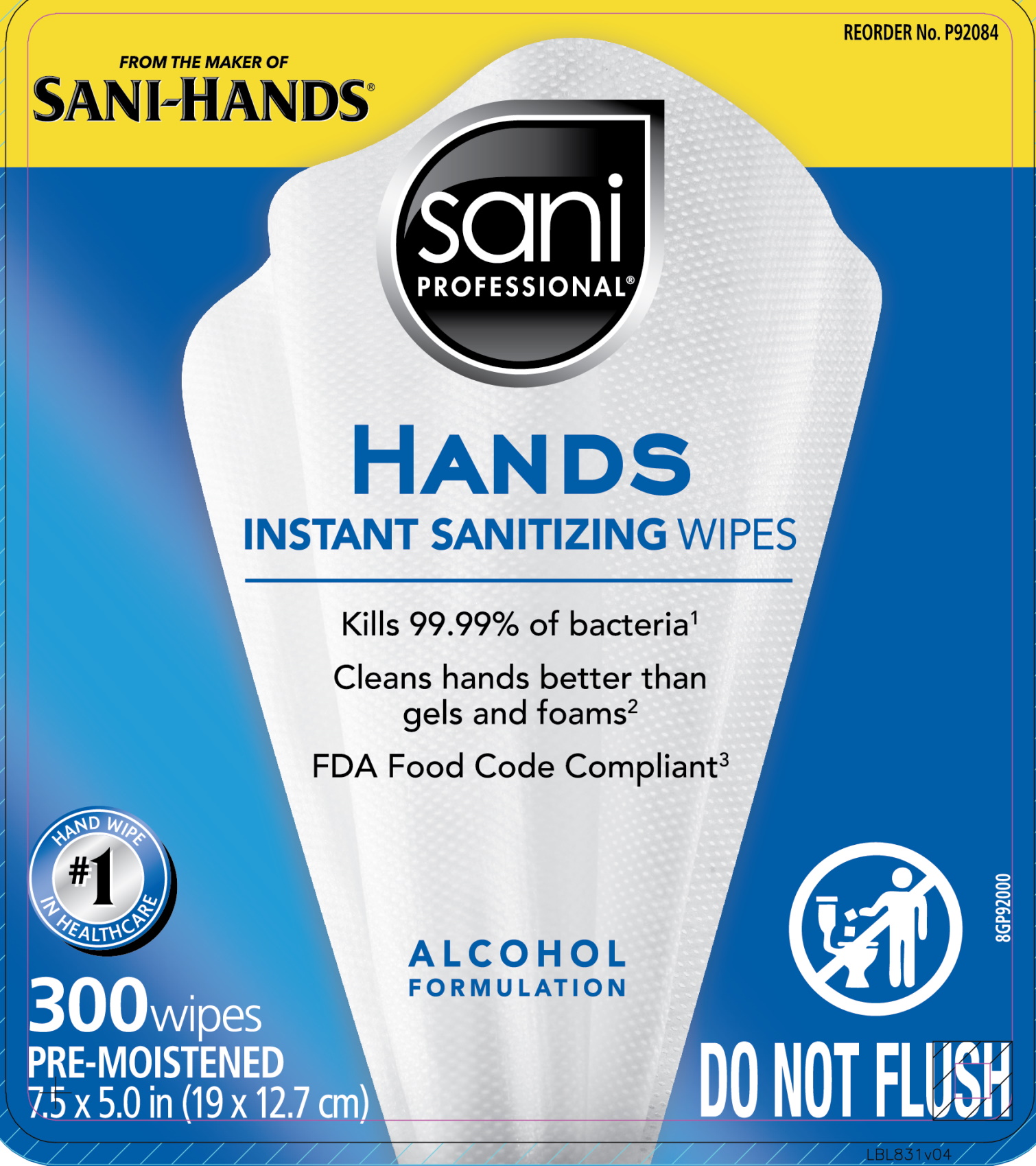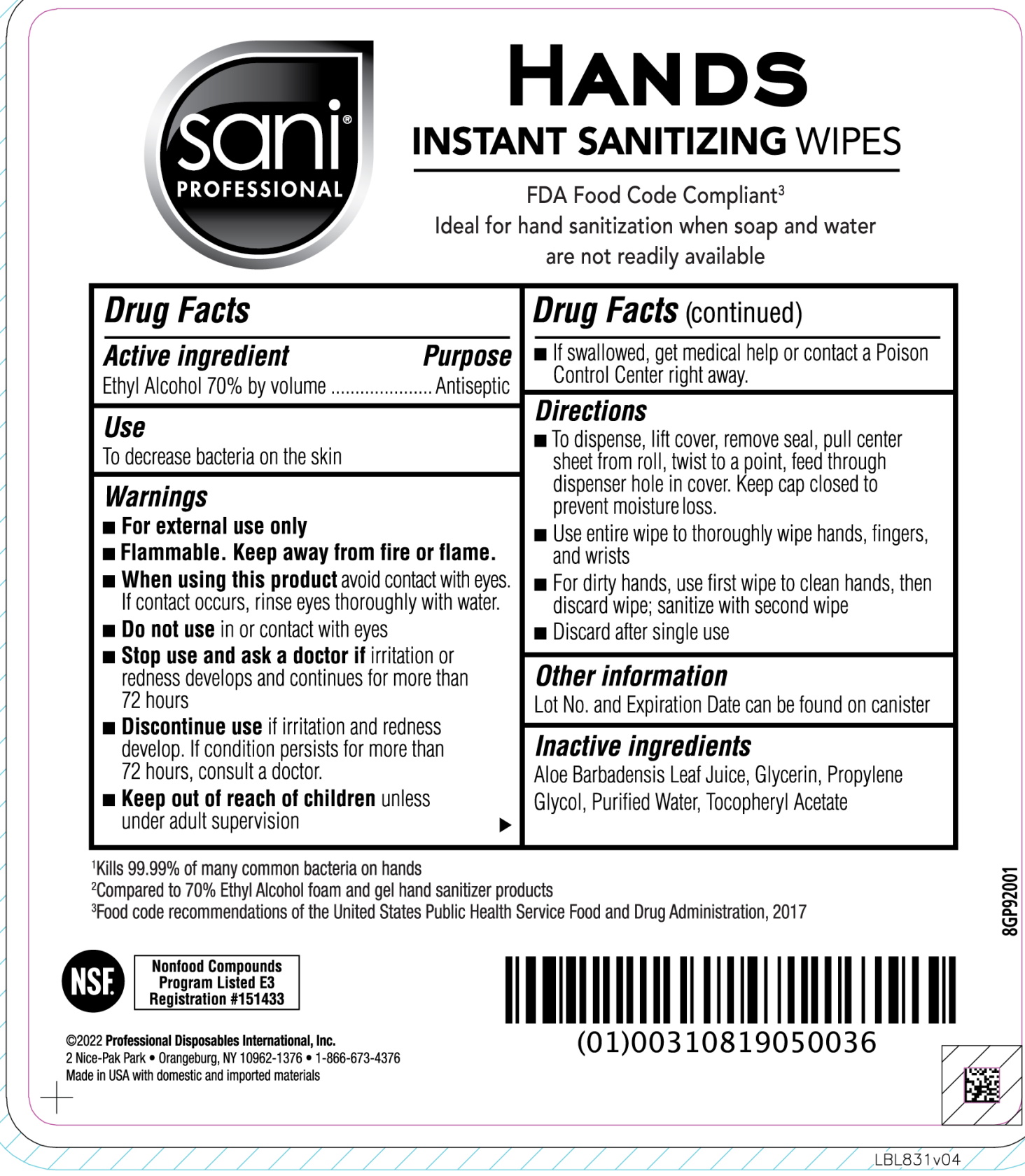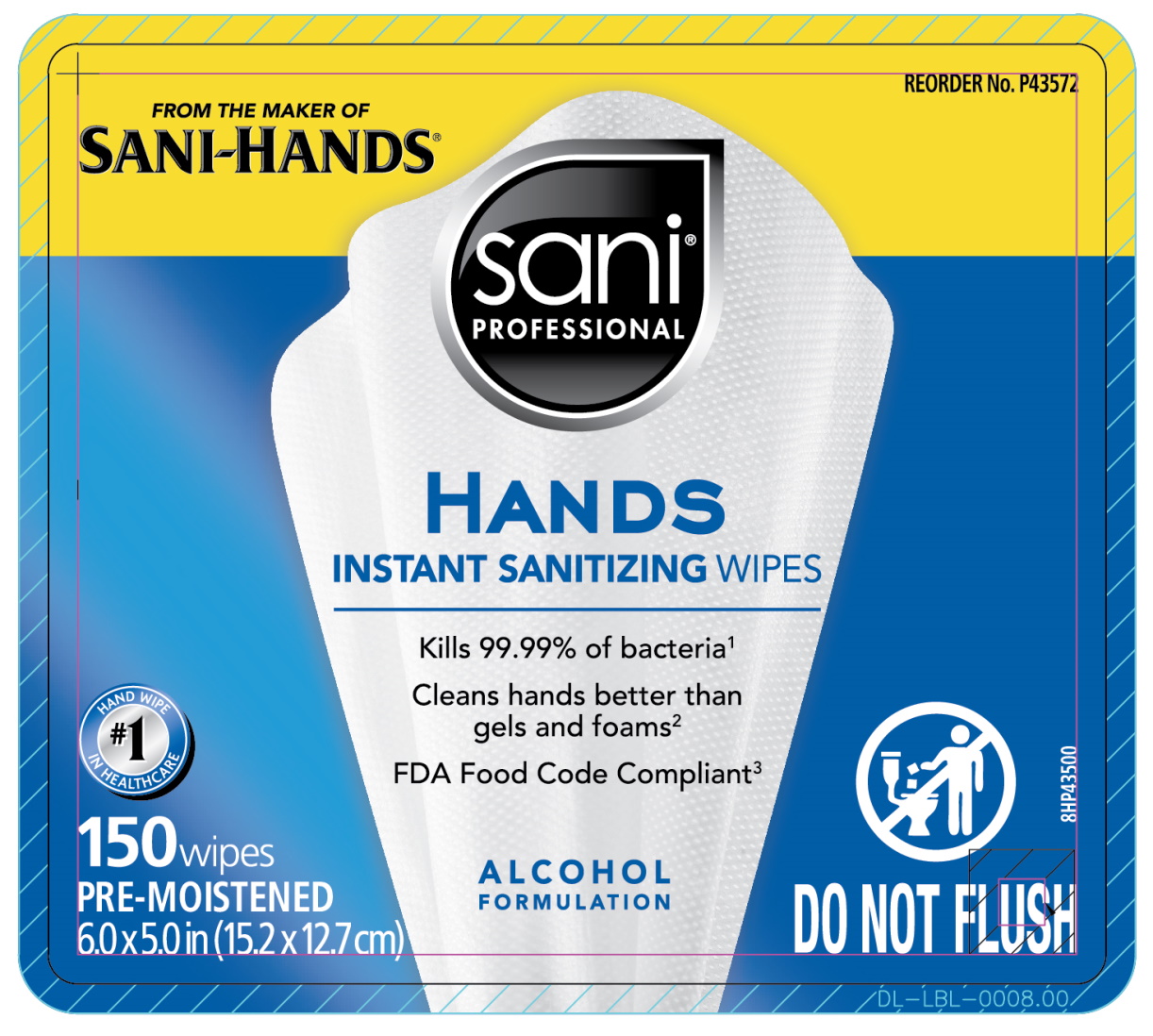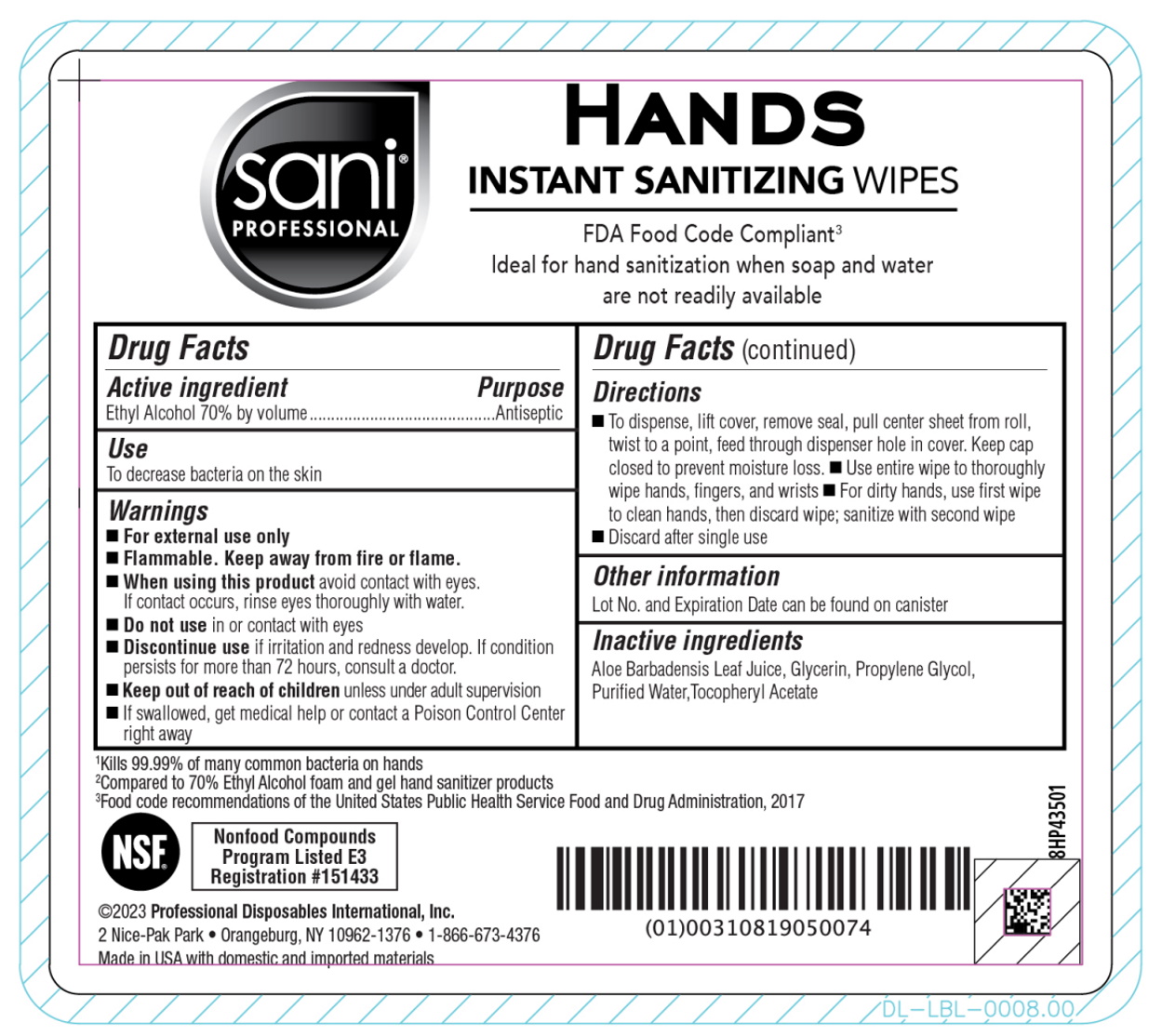 DRUG LABEL: Sani Professional Hands Instant Sanitizing Wipes
NDC: 10819-6006 | Form: CLOTH
Manufacturer: Professional Disposables International, Inc.
Category: otc | Type: HUMAN OTC DRUG LABEL
Date: 20240820

ACTIVE INGREDIENTS: ALCOHOL 0.7 mL/1 mL
INACTIVE INGREDIENTS: GLYCERIN; WATER; ALOE VERA LEAF; ALPHA-TOCOPHEROL ACETATE; PROPYLENE GLYCOL

Sani Professional Hands Instant Sanitizing Wipes

Active Ingredient

Ethyl Alcohol 70% by volume

Purpose

Antiseptic

Uses

To decrease bacteria on the skin

Warnings

For external use only

Flammable. Keep away from fire or flame

When using this product avoid contact with eyes. If contact occurs, rinse eyes thoroughly with water.

Do not use in or contact with eyes

Discontinue use if irritation and redness develop. If condition persists for more than 72 hours, consult a doctor.

Keep out of reach of children unless under adult supervision

If swallowed, get medical help or contact a Poison Control Center right away

Directions

Canister:

to dispense, lift cover, remove seal, pull center sheet from roll, twist to a point, feed through dispenser hole in cover. Keep cap closed to prevent moisture loss.

use entire wipe to thoroughly wipe hands, fingers, and wrists

for dirty hands, use first wipe to clean hands, then discard wipe; sanitize with second wipe

discard after single use

Packet:

open packet

use entire wipe to thoroughly wipe hands, fingers, and wrists

to sanitize, use multiple wipes

discard after single use

Other information

Lot No. and Expiration Date can be found on canister

Inactive ingredients

aloe barbadensis leaf juice, glycerin, propylene glycol, purified water, tocopheryl acetate

Principal display panel

Packet

Canister, 150ct

Canister, 300ct